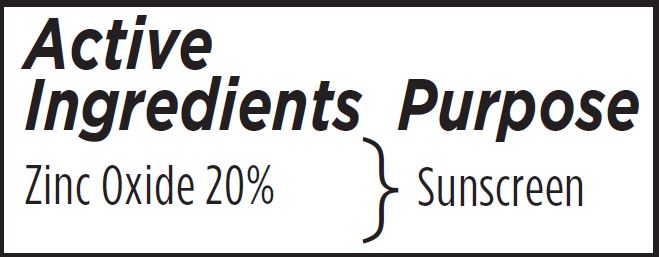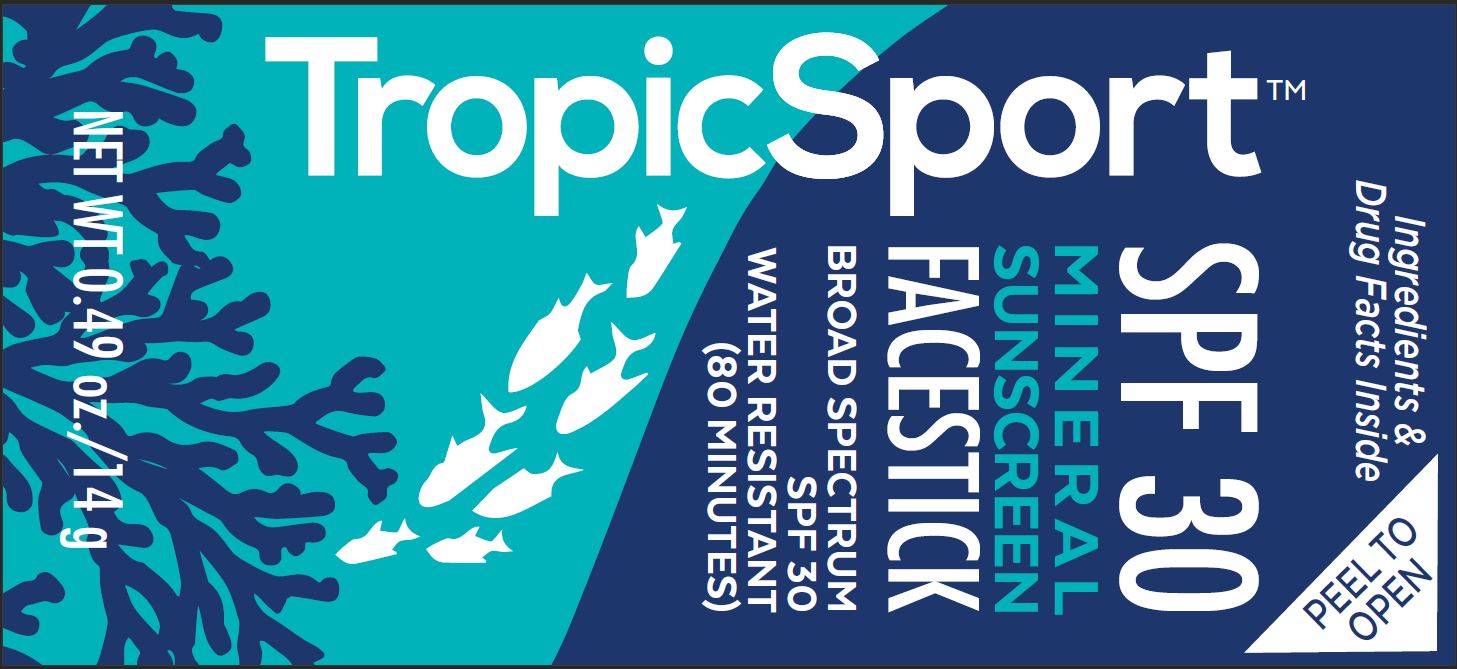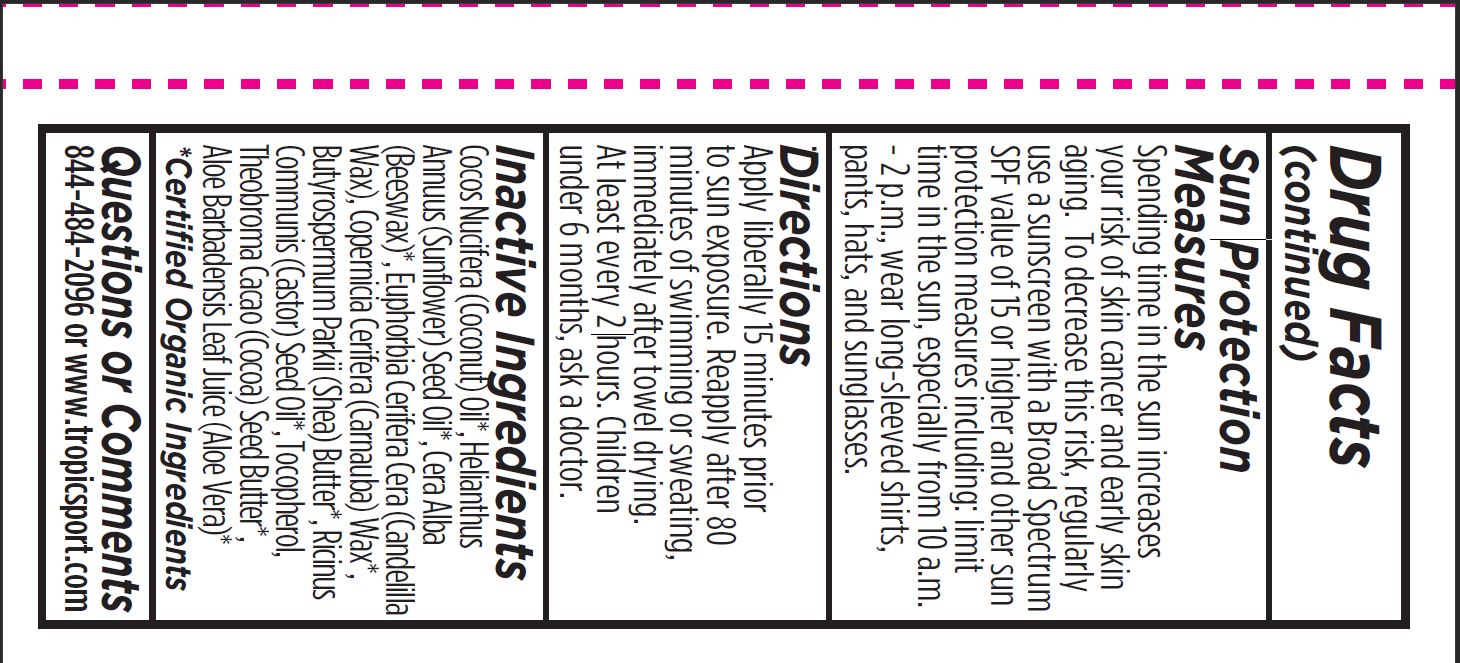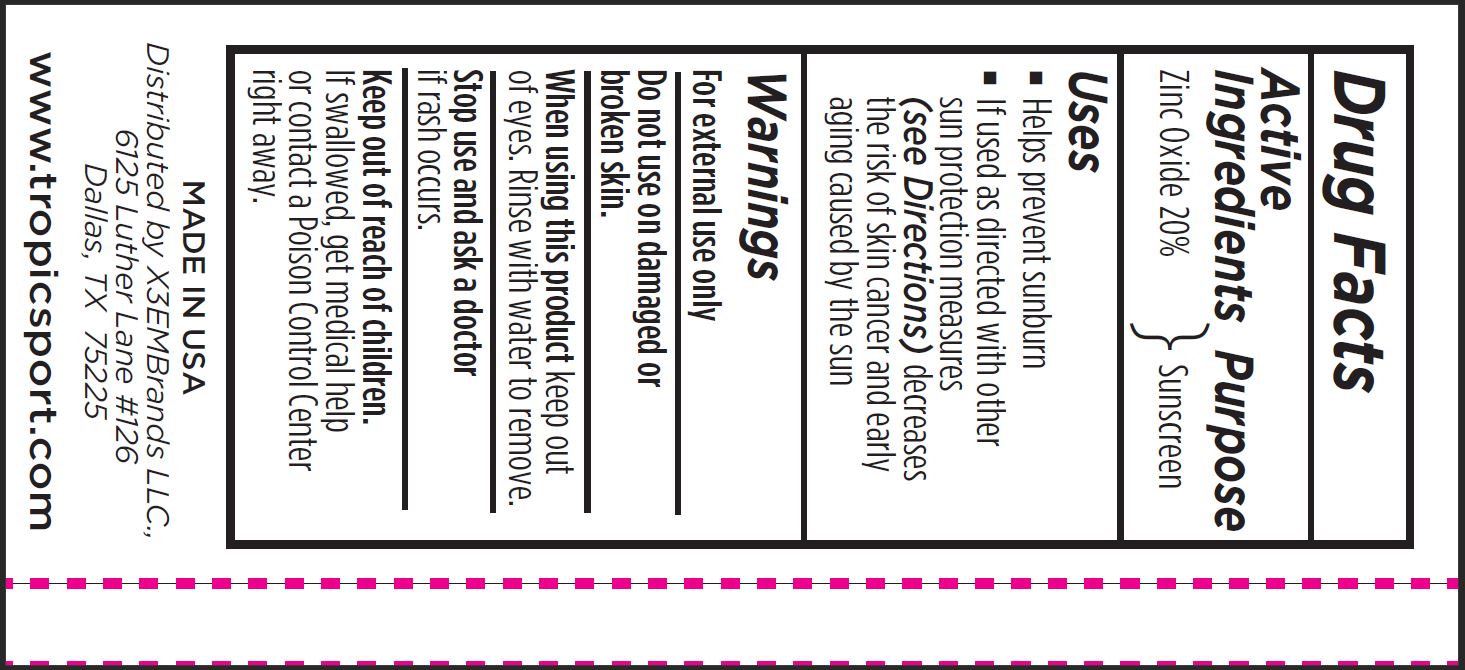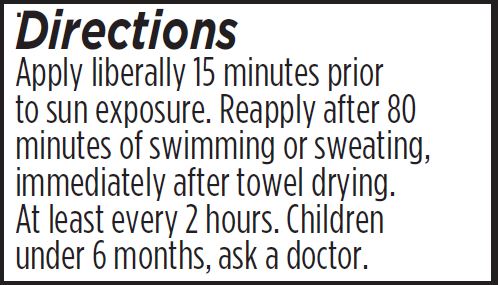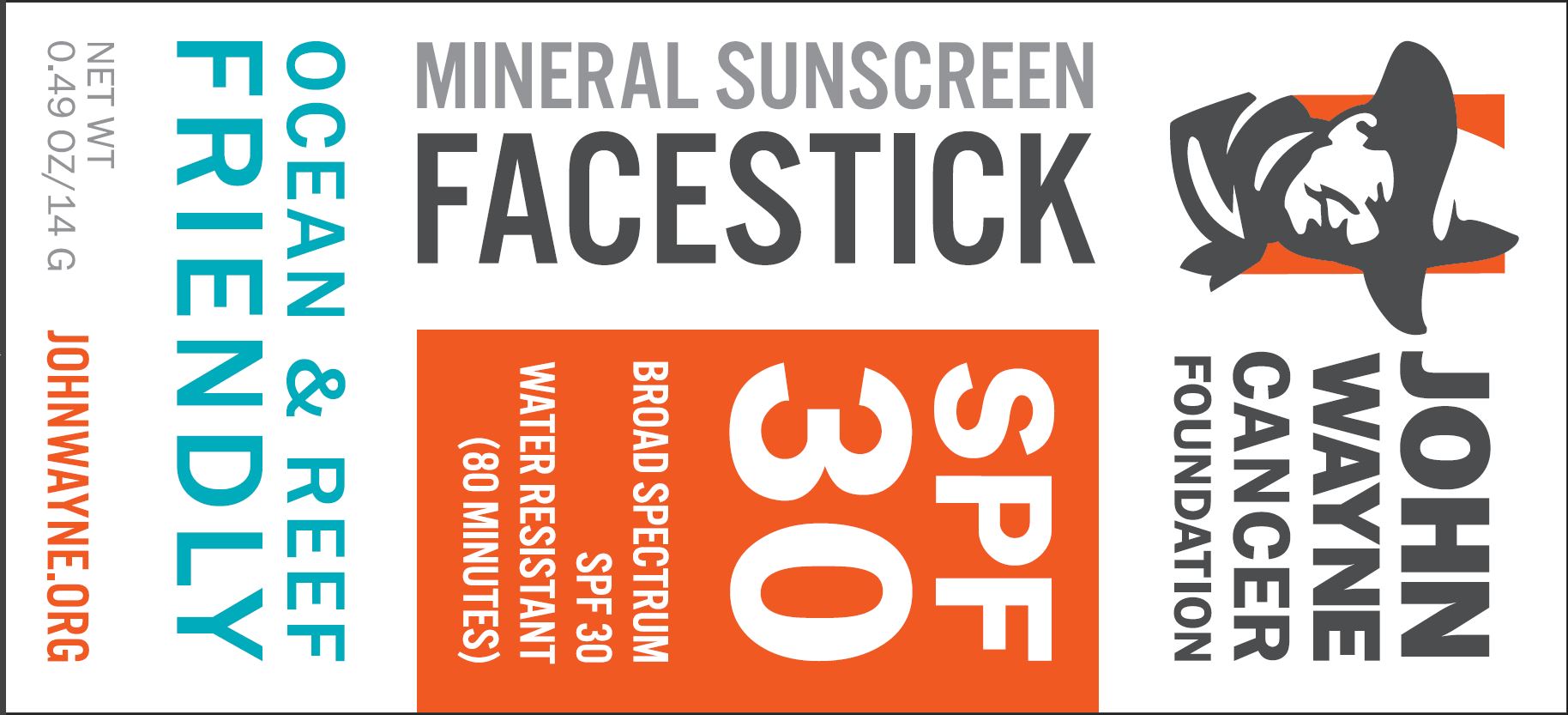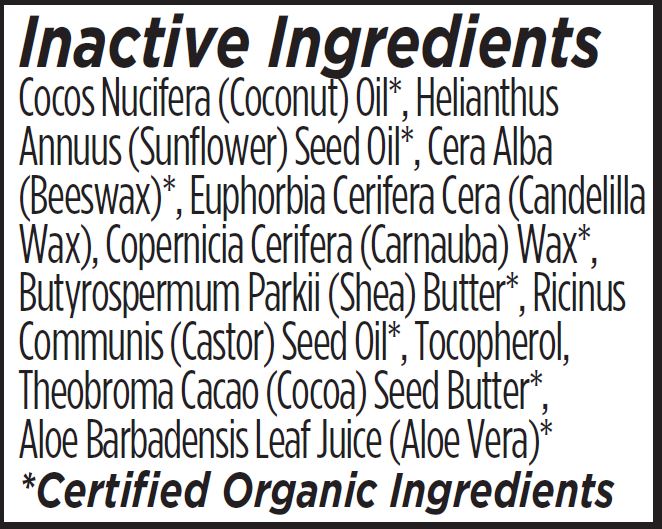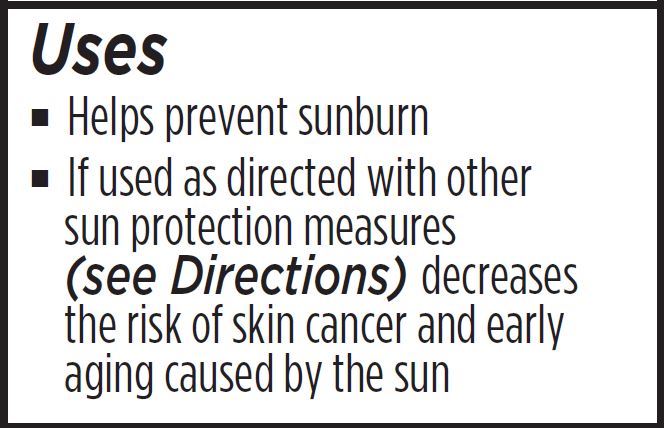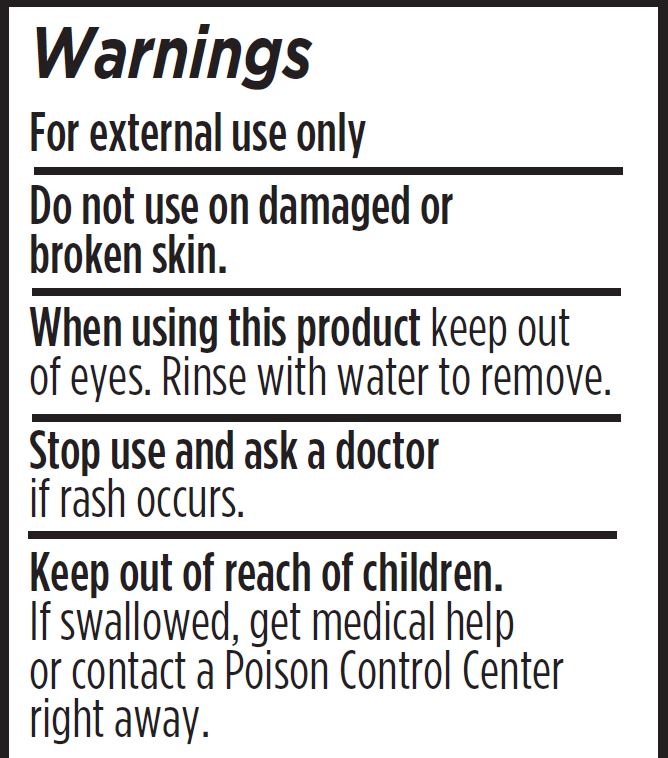 DRUG LABEL: John Wayne Cancer Foundation Mineral Sunscreen Facestick SPF 30
NDC: 62932-256 | Form: STICK
Manufacturer: Private Label Select Ltd CO
Category: otc | Type: HUMAN OTC DRUG LABEL
Date: 20211230

ACTIVE INGREDIENTS: ZINC OXIDE 20 g/100 g
INACTIVE INGREDIENTS: SUNFLOWER OIL; WHITE WAX; CANDELILLA WAX; SHEA BUTTER; .ALPHA.-TOCOPHEROL, D-; .BETA.-TOCOPHEROL; CARNAUBA WAX; .GAMMA.-TOCOPHEROL; .DELTA.-TOCOPHEROL; COCOA BUTTER; COCONUT OIL; CASTOR OIL; ALOE VERA LEAF

X3EMBrands, LLC John Wayne Cancer Foundation Mineral Sunscreen Facestick SPF 30